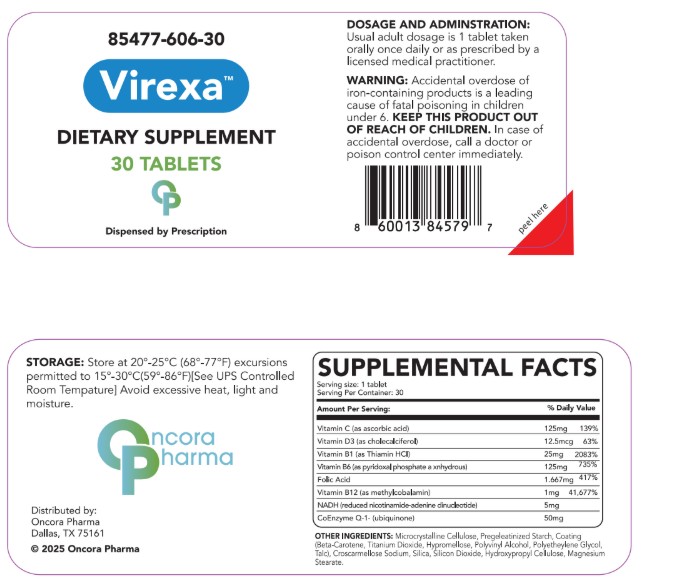 DRUG LABEL: Virexa
NDC: 85477-606 | Form: TABLET
Manufacturer: Oncora Pharma, LLC
Category: prescription | Type: HUMAN PRESCRIPTION DRUG LABEL
Date: 20250905

ACTIVE INGREDIENTS: ASCORBIC ACID 125 mg/1 1; CHOLECALCIFEROL 12.5 ug/1 1; THIAMINE HCL 25 mg/1 1; PYRIDOXAL PHOSPHATE ANHYDROUS 125 mg/1 1; FOLIC ACID 1.667 mg/1 1; METHYLCOBALAMIN 1 mg/1 1; NICOTINAMIDE ADENINE DINUCLEOTIDE 5 mg/1 1; UBIQUINONE 50 mg/1 1

Virexa

DOSAGE AND ADMINISTRATION

Usual Adult dose is 1 tablet once or twice daily or as prescribed by a licensed medical practitioner.

WARNINGS

Accidental overdose of iron-containing products is a leading cause of fatal poisoninng in children under 6.

Keep out of reach of children.

In case of accidental overdose, call a doctor or poison control immediately.

INDICATIONS AND USAGE

Virexa is a multivitamin with folic acid dispensed by prescription only.

HOW SUPPLIED

Store at 20°-25° C (68°-77°F) exursions permitted to 15°-30°C (59°F-86°F). Keep in cool dry place. [See USP Controlled Room Temperature] Avoid excessive heat, light, moisture and exceeding 85% humidity.

DESCRIPTION

Active Ingredients: VItamin C, Vitamin D3, Vitamin B1, Vitamin B6, Vitamin B12, Folic Acid, NADH, Ubiquinone.

Inactive Ingredients: Microcrystalline Cellulose, Pregeleatinized Starch, Coating (Beta-Carotene, Titanium Dioxide, Hypromellose, Polyvinyl Alcohol, Polyethylene Glycol, Talc), Croscarmellose Sodium, Silica, Silicon Dioxide, Hydroxypropyl Cellulose, Magnesium Stearate.